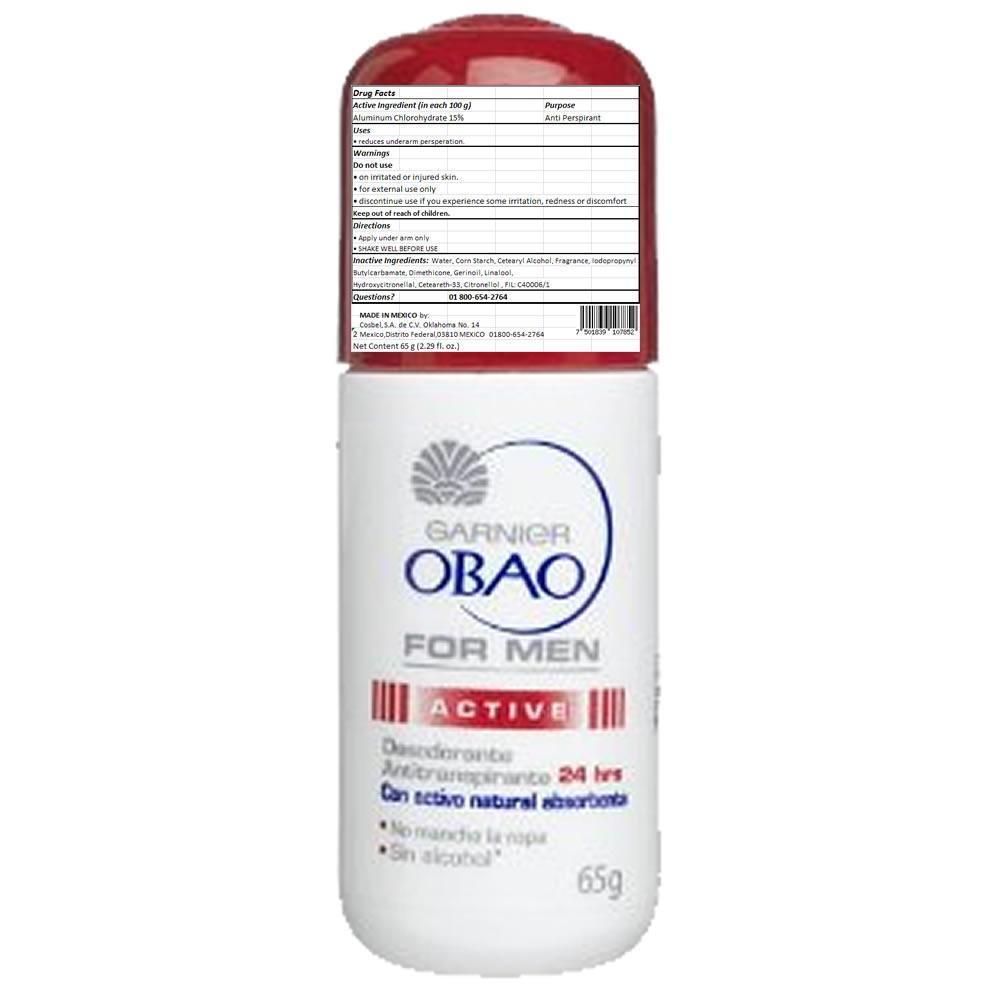 DRUG LABEL: Obao
NDC: 51769-127 | Form: LIQUID
Manufacturer: ALL NATURAL DYNAMICS
Category: otc | Type: HUMAN OTC DRUG LABEL
Date: 20130819

ACTIVE INGREDIENTS: ALUMINUM CHLOROHYDRATE 15 g/100 g
INACTIVE INGREDIENTS: WATER; STARCH, CORN; CETOSTEARYL ALCOHOL; DIMETHICONE; LINALOOL, DL-; GERANIOL; .BETA.-CITRONELLOL, (+/-)-

Drug Facts

Warnings:

For External Use Only. Do Not Apply On Irritated Or Injured Skin. Discontinue Use If You Experience Some Irritation, Redness Or Discomfort.

Active Ingredient:

Aluminum Chlorohydrate 15%

Purpose

Antiperspirant

Keep Out Of The Reach Of Children

USE:

reduces underarm persperation

Directions:

Apply under arm only.

SHAKE WELL BEFORE USE.

Inactive Ingredients:

water, corn starch, cetearyl alcohol, fragrance, eugenol, ethylparaben, dimethicone, benzyl alcohol, linalool, benzyl benzoate, benzyl salicylate, alpha-isomethyl ionone, geraniol, ceteareth-33, methylparaben, butylphenyl methylpropional, citronellol, hexyl cinnamal